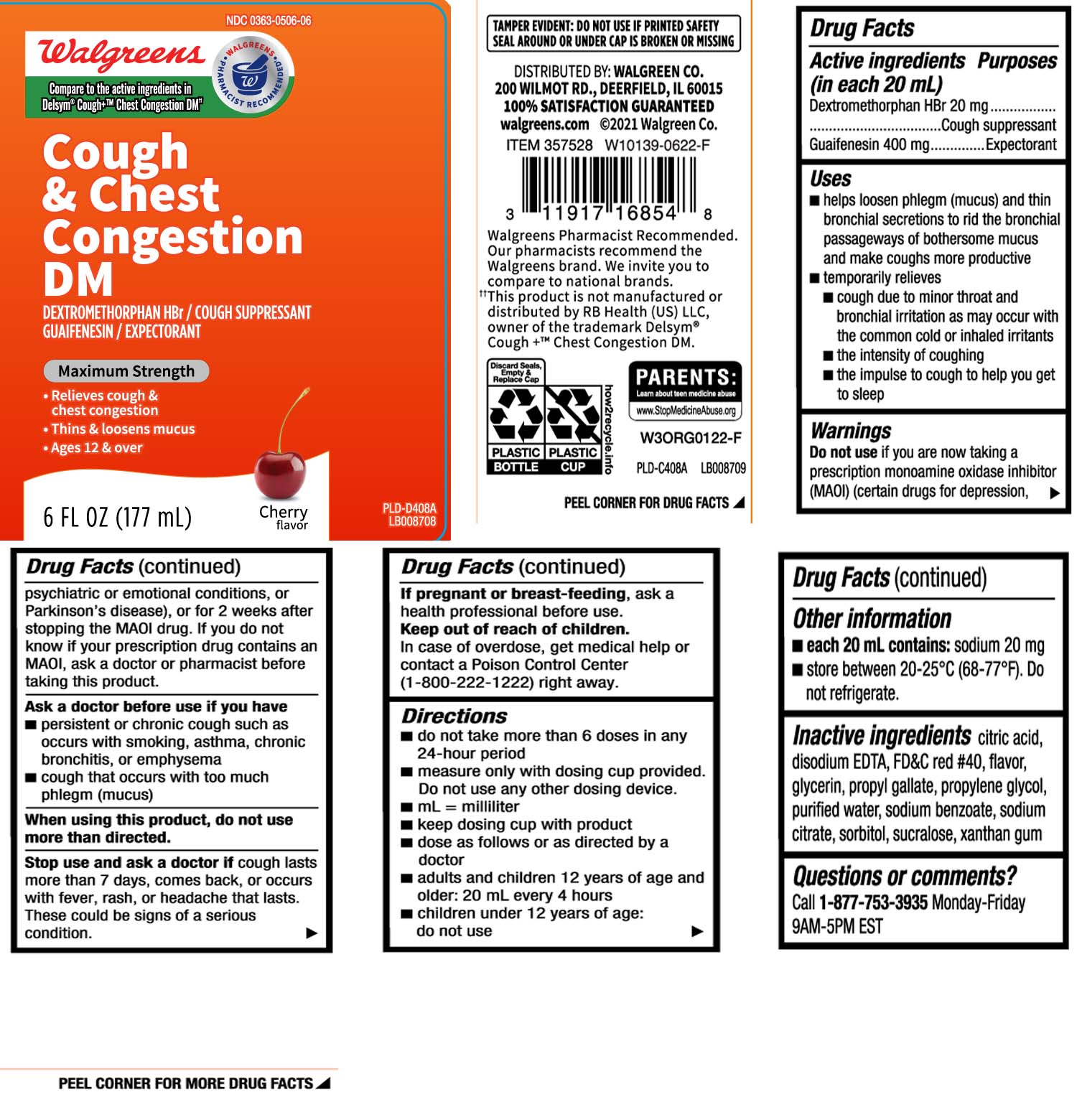 DRUG LABEL: Cough and Chest Congestion DM
NDC: 0363-0506 | Form: LIQUID
Manufacturer: Walgreens
Category: otc | Type: HUMAN OTC DRUG LABEL
Date: 20240621

ACTIVE INGREDIENTS: DEXTROMETHORPHAN HYDROBROMIDE 20 mg/20 mL; GUAIFENESIN 400 mg/20 mL
INACTIVE INGREDIENTS: ANHYDROUS CITRIC ACID; GLYCERIN; PROPYLENE GLYCOL; WATER; SUCRALOSE; XANTHAN GUM; FD&C RED NO. 40; EDETATE CALCIUM DISODIUM; PROPYL GALLATE; SODIUM BENZOATE; SODIUM CITRATE; SORBITOL

Drug Facts

Active ingredients (in each 20 mL)

Dextromethorphan HBr 20 mg

Guaifenesin 400 mg

Purposes

Cough suppressant

Expectorant

Uses

- helps loosen phlegm (mucus) and thin bronchial secretions to rid the bronchial passageways of bothersome mucus and make coughs more productive
- temporarily relieves:
  - cough due to minor throat and bronchial irritation as may occur with the common cold or inhaled irritants
  - the intensity of coughing
  - the impulse to cough to help you get to sleep

Warnings

Do not use

if you are now taking a prescription monoamine oxidase inhibitor (MAOI) (certain drugs for depression, psychiatric or emotional conditions, or Parkinson's disease), or for 2 weeks after stopping the MAOI drug. If you do not know if your prescription drug contains an MAOI, ask a doctor or pharmacist before taking this product.

Ask a doctor before use if you have

- persistent or chronic cough such as occurs with smoking, asthma, chronic bronchitis, or emphysema
- cough that occurs with too much phlegm (mucus)

When using this product,

do not use more than directed.

Stop use and ask a doctor if

cough lasts more than 7 days, comes back, or occurs with fever, rash or headache that lasts. These could be signs of a serious condition.

If pregnant or breast-feeding,

ask a health professional before use.

Keep out of reach of children

In case of overdose, get medical help or contact a Poison Control Center (1-800-222-1222) right away.

Directions

- do not take more than 6 doses in any 24-hour period
- measure only with dosing cup provided. Do not use any other dosing device.
- keep dosing cup with product
- mL = milliliter
- dose as follows or as directed by a doctor
- adults and children 12 years of age and older: 20 mL every 4 hours
- children under 12 years of age: do not use

Other information

- each 20 mL contains: sodium 20 mg
- store between 20-25ºC (68-77ºF). Do not refrigerate.

Inactive ingredients

anhydrous citric acid, disodium EDTA, FD&C red #40, flavor, glycerin, propyl gallate, propylene glycol, purified water, sodium benzoate, sodium citrate, sorbitol, sucralose, xanthan gum

Question or comments?

Call 1-877-753-3935 Monday-Friday 9AM-5PM EST

Principal Display Panel

Compare to the active ingredients in Delsym® Cough+™ Chest Congestion DM††

Cough & Chest

Congestion DM

DEXTROMETHORPHAN HBr / COUGH SUPPRESSANT

GUAIFENESIN / EXPECTORANT

Maximum Stength

- Relieves cough & chest congestion
- Thins & loosens mucus
- For ages 12 & over

Cherry flavor

FL OZ (mL)

TAMPER EVIDENT: DO NOT USE IF PRINTED SAFETY SEAL AROUND AND UNDER CAP IS BROKEN OR MISSING

††This product is not manufactured or distributed by RB Health (US) LLC, owner of the trademark Delsym® Cough+™ Chest Congestion DM.

DISTRIBUTED BY: WALGREEN CO.

200 WILMOT RD., DEERFIELD, IL 60015

walgreens.com

Package Label

WALGREENS Cough and Chest Congestion DM Cherry Flavor